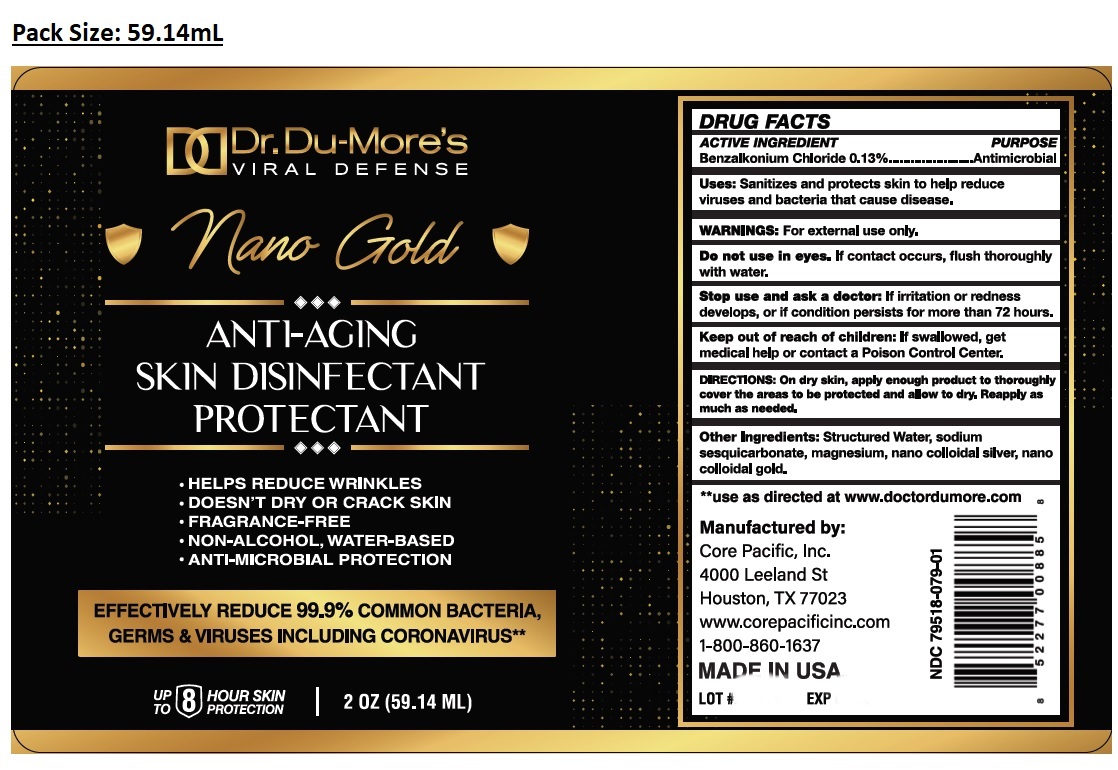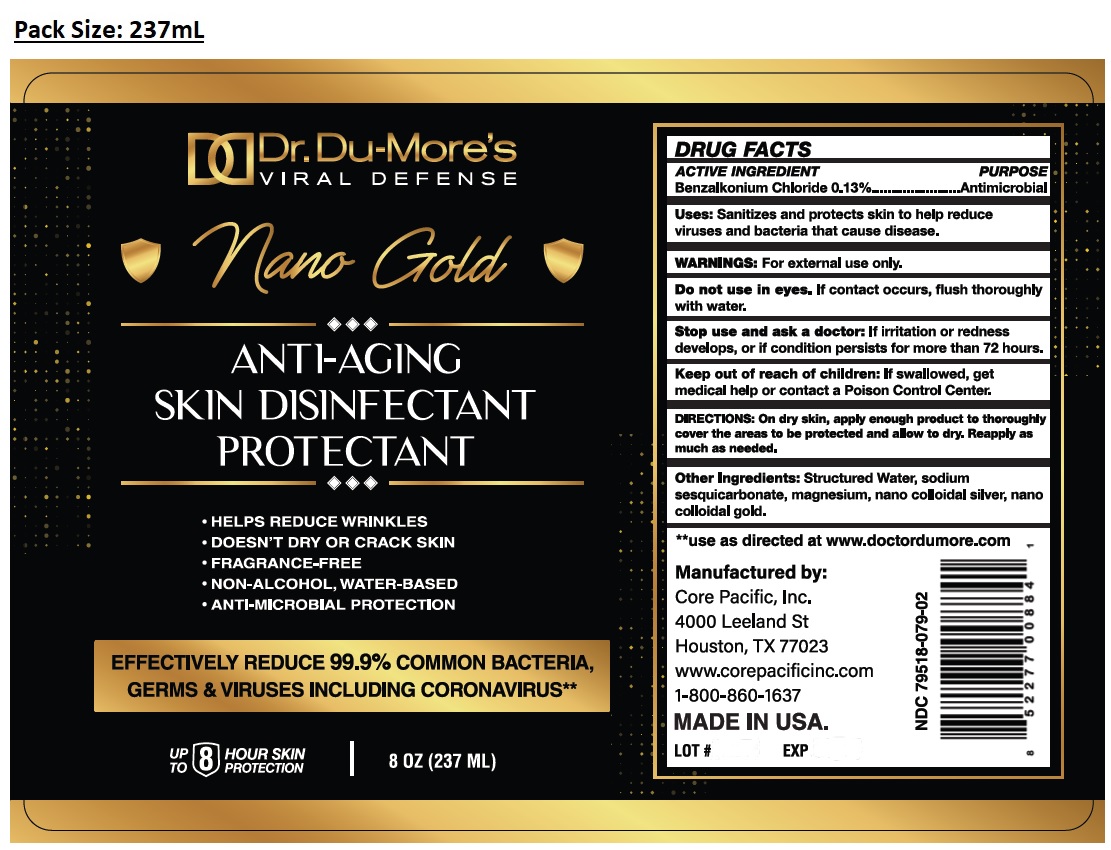 DRUG LABEL: Dr. Du-Mores VIRAL DEFENSE Nano Gold ANTI-AGING SKIN DISINFECTANT PROTECTANT
NDC: 79518-079 | Form: LIQUID
Manufacturer: Core Pacific, Inc.
Category: otc | Type: HUMAN OTC DRUG LABEL
Date: 20210105

ACTIVE INGREDIENTS: BENZALKONIUM CHLORIDE 0.13 g/100 mL
INACTIVE INGREDIENTS: WATER; SODIUM SESQUICARBONATE; MAGNESIUM; SILVER; GOLD

Dr. Du-More's VIRAL DEFENSE Nano Gold ANTI-AGING SKIN DISINFECTANT PROTECTANT

ACTIVE INGREDIENT

Benzalkonium Chloride 0.13%

PURPOSE

Antimicrobial

Uses:

Sanitizes and protects skin to help reduce viruses and bacteria that cause disease.

WARNINGS:

For external use only.

Do not use in eyes. If contact occurs, flush thoroughly with water.

Stop use and ask a doctor: If irritation or redness develops, or if condition persists for more than 72 hours.

Keep out of reach of children: If swallowed, get medical help or contact a Poison Control Center.

DIRECTIONS:

On dry skin, apply enough product to thoroughly cover the areas to be protected and allow to dry. Reapply as much as needed.

Other Ingredients:

Structured Water, sodium sesquicarbonate, magnesium, nano colloidal silver, nano colloidal gold.

• HELPS REDUCE WRINKLES

• DOESN'T DRY OR CRACK SKIN

• FRAGRANCE-FREE

• NON-ALCOHOL, WATER-BASED

• ANTI-MICROBIAL PROTECTION

EFFECTIVELY REDUCE 99.9% COMMON BACTERIA, GERMS & VIRUSES INCLUDING CORONAVIRUS**

UP TO 8 HOUR SKIN PROTECTION

**use as directed at www.doctordumore.com

Manufactured by:

Core Pacific, Inc.

4000 Leeland, St

Houston, TX 77023

www.corepacificinc.com

1-800-860-1637

MADE IN USA.